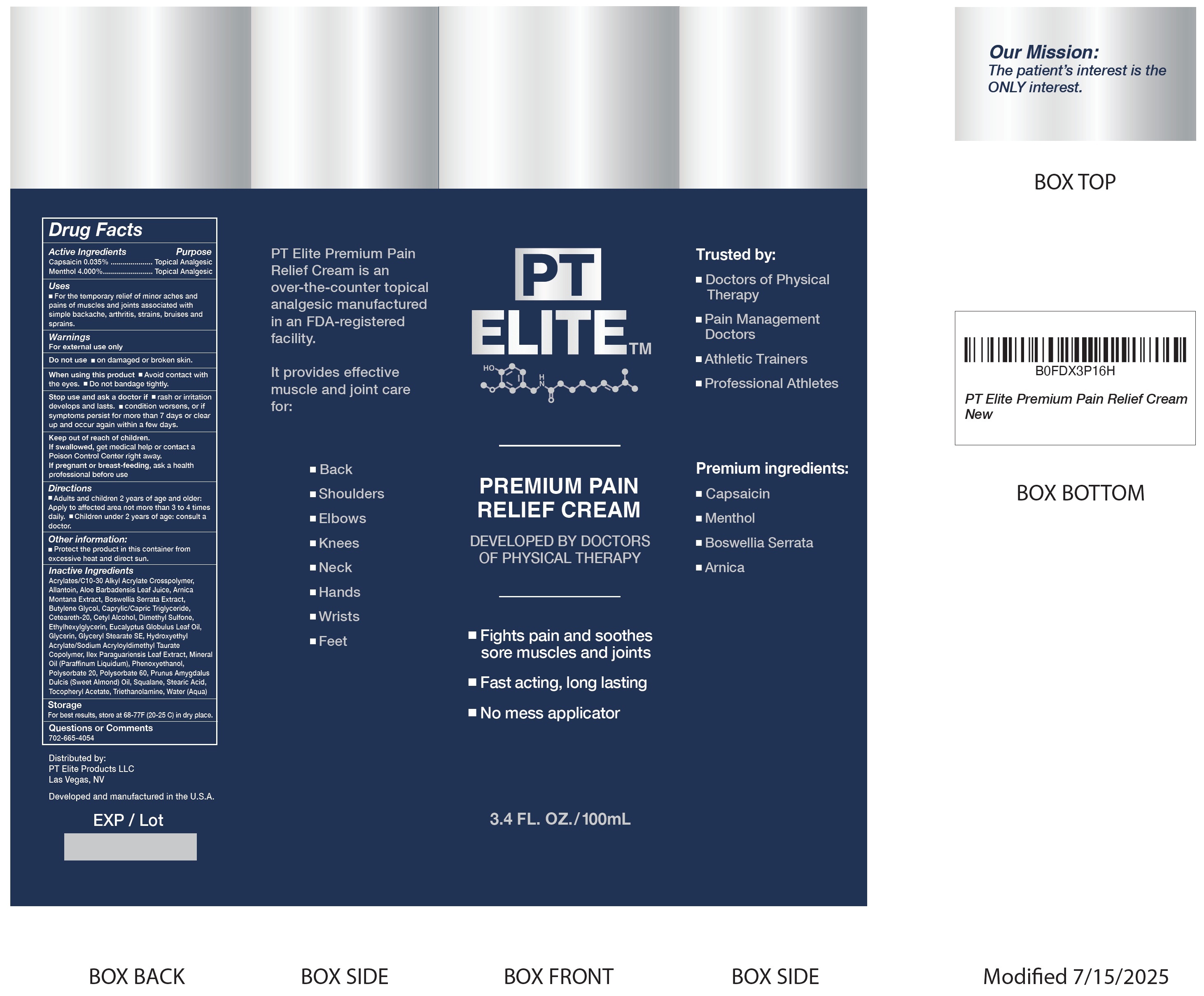 DRUG LABEL: PT Elite Premium Pain Relief
NDC: 85808-615 | Form: CREAM
Manufacturer: PT ELITE PRODUCTS LLC
Category: otc | Type: HUMAN OTC DRUG LABEL
Date: 20250723

ACTIVE INGREDIENTS: CAPSAICIN 0.35 mg/1 mL; MENTHOL 40 mg/1 mL
INACTIVE INGREDIENTS: ALLANTOIN; ALOE VERA LEAF JUICE; ARNICA MONTANA WHOLE; INDIAN FRANKINCENSE; BUTYLENE GLYCOL; MEDIUM-CHAIN TRIGLYCERIDES; CETEARETH-20; CETYL ALCOHOL; DIMETHYL SULFONE; ETHYLHEXYLGLYCERIN; EUCALYPTUS OIL; GLYCERIN; GLYCERYL STEARATE SE; PHENOXYETHANOL; POLYSORBATE 20; POLYSORBATE 60; ALMOND OIL; SQUALANE; STEARIC ACID; .ALPHA.-TOCOPHEROL ACETATE; TROLAMINE; WATER

PT Elite Premium Pain Relief Cream

Active Ingredients

Capsaicin 0.035%
Menthol 4.000 %

Purpose

Topical Analgesic

Uses

- For the temporary relief of minor aches and pains of muscles and joints associated with simple backache, arthritis, strains, bruises and sprains.

Warnings

For external use only

Do not use

- on damaged or broken skin.

When using this product

- Avoid contact with the eyes.
- Do not bandage tightly.

Stop use and ask a doctor if

- rash or irritation develops and lasts.
- condition worsens, or if symptoms persist for more than 7 days or clear up and occur again within a few days.

Keep out of reach of children.

If swallowed, get medical help or contact a Poison Control Center right away.

If pregnant or breast-feeding,

ask a health professional before use

Directions

- Adults and children 2 years of age and older: Apply to affected area not more than 3 to 4 times daily.
- Children under 2 years of age: consult a doctor.

Other information:

- Protect the product in this container from excessive heat and direct sun.

Inactive Ingredients

Acrylates/C10-30 Alkyl Acrylate Crosspolymer, Allantoin, Aloe Barbadensis Leaf Juice, Arnica Montana Extract, Boswellia Serrata Extract, Butylene Glycol, Caprylic/Capric Triglyceride, Ceteareth-20, Cetyl Alcohol, Dimethyl Sulfone, Ethylhexylglycerin, Eucalyptus Globulus Leaf Oil, Glycerin, Glyceryl Stearate SE, Hydroxyethyl Acrylate/Sodium Acryloyldimethyl Taurate Copolymer, Ilex Paraguariensis Leaf Extract, Mineral Oil (Paraffinum Liquidum), Phenoxyethanol, Polysorbate 20, Polysorbate 60, Prunus Amygdalus Dulcis (Sweet Almond) Oil, Squalane, Stearic Acid, Tocopheryl Acetate, Triethanolamine, Water (Aqua)

Storage

For best results, store at 68-77F (20-25 C) in dry place.

Questions or Comments

702-665-4054